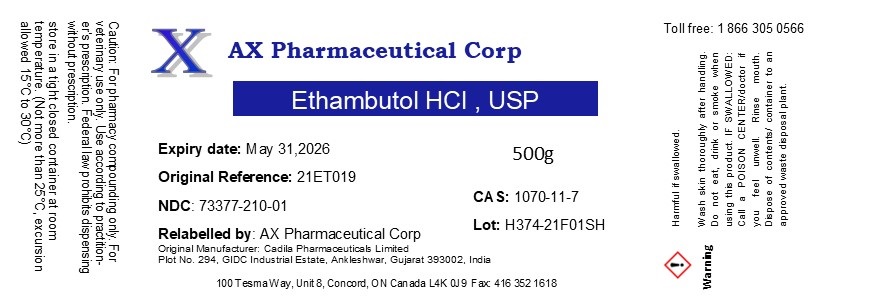 DRUG LABEL: Ethambutol HCl
NDC: 73377-210 | Form: POWDER
Manufacturer: AX Pharmaceutical Corp
Category: other | Type: BULK INGREDIENT - ANIMAL DRUG
Date: 20221109

ACTIVE INGREDIENTS: ETHAMBUTOL HYDROCHLORIDE 1 g/1 g

Ethambutol HCl